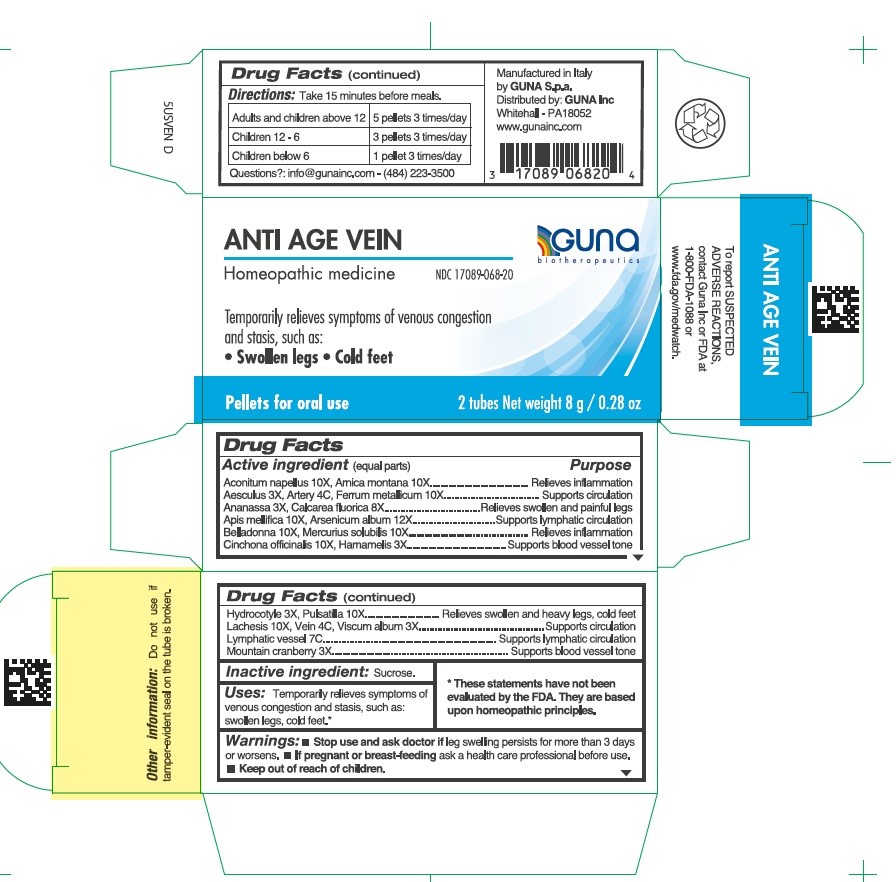 DRUG LABEL: ANTI AGE VEIN
NDC: 17089-068 | Form: PELLET
Manufacturer: Guna spa
Category: homeopathic | Type: HUMAN OTC DRUG LABEL
Date: 20231102

ACTIVE INGREDIENTS: ACONITUM NAPELLUS 10 [hp_X]/4 g; HORSE CHESTNUT 3 [hp_X]/4 g; PINEAPPLE 3 [hp_X]/4 g; APIS MELLIFERA 10 [hp_X]/4 g; ARNICA MONTANA 10 [hp_X]/4 g; ARSENIC TRIOXIDE 12 [hp_C]/4 g; SUS SCROFA ARTERY 4 [hp_C]/4 g; ATROPA BELLADONNA 10 [hp_X]/4 g; CALCIUM FLUORIDE 8 [hp_X]/4 g; CINCHONA OFFICINALIS BARK 10 [hp_X]/4 g; IRON 10 [hp_X]/4 g; WITCH HAZEL 3 [hp_X]/4 g; CENTELLA ASIATICA 3 [hp_X]/4 g; LACHESIS MUTA VENOM 10 [hp_X]/4 g; SUS SCROFA SMALL INTESTINE MUCOSA LYMPH FOLLICLE 7 [hp_C]/4 g; MERCURY 10 [hp_X]/4 g; CRANBERRY 3 [hp_X]/4 g; PULSATILLA VULGARIS 10 [hp_X]/4 g; SUS SCROFA VEIN 4 [hp_C]/4 g; VISCUM ALBUM FRUIT 3 [hp_X]/4 g
INACTIVE INGREDIENTS: SUCROSE 3.5 g/4 g

ANTI AGE VEIN

ACTIVE INGREDIENT

Aconitum napellus 10X, Arnica montana 10X.....................................Relieves inflammation

Aesculus hippocastanum 3X, Artery 4C, Ferrum metallicum 10X.......Supports circulation

Ananassa 3X, Calcarea fluorica 8X.....................................................Relieves swollen and painful legs

Apis mellifica 10X, Arsenicum album 12X...........................................Supports lymphatic circulation

Belladonna 10X, Mercurius solubilis 10X............................................Relieves inflammation

Cinchona officinalis 10X, Hamamelis 3X.............................................Supports blood vessel tone

Hydrocotyle 3X, Pulsatilla 10X............................................................Relieves swollen and heavy legs, cold feet

Lachesis 10X, Vein 4C, Viscum album 3X..........................................Supports circulation

Lymphatic vessel 7C...........................................................................Supports lymphatic circulation

Mountain cranberry 3X........................................................................Supports blood vessel tone

PURPOSE

Temporarily relieves symptoms of venous congestion and stasis, such as:

- swollen legs
- cold feet

Stop use and ask doctor if symptoms persist more than 5 days or worsen.
If pregnant or breast-feeding ask a health care professional before use.
Keep out of reach of children.

PREGNANCY OR BREAST FEEDING

If pregnant or breast-feeding ask a health professional before use.

KEEP OUT OF REACH OF CHILDREN

Keep this and all medicines out of reach of children

DOSAGE AND ADMINISTRATION

Take 15 minutes before meals
Adults and children 12 years and older 5 pellets 3 times per day
Children between 12 years and 6 years of age 3 pellets 3 times per day
Children under 6 years Ask a physician

Questions?: info@gunainc.com
tel. (484) 223-3500

Directions

- Turn tube upside down and rotate cap to release pellets into cap.
- Unscrew cap and without touching pellets tip them into the mouth under the tongue.
- Allow to dissolve
- Take 15 minutes before meals.

Inactive ingredient: Sucrose.